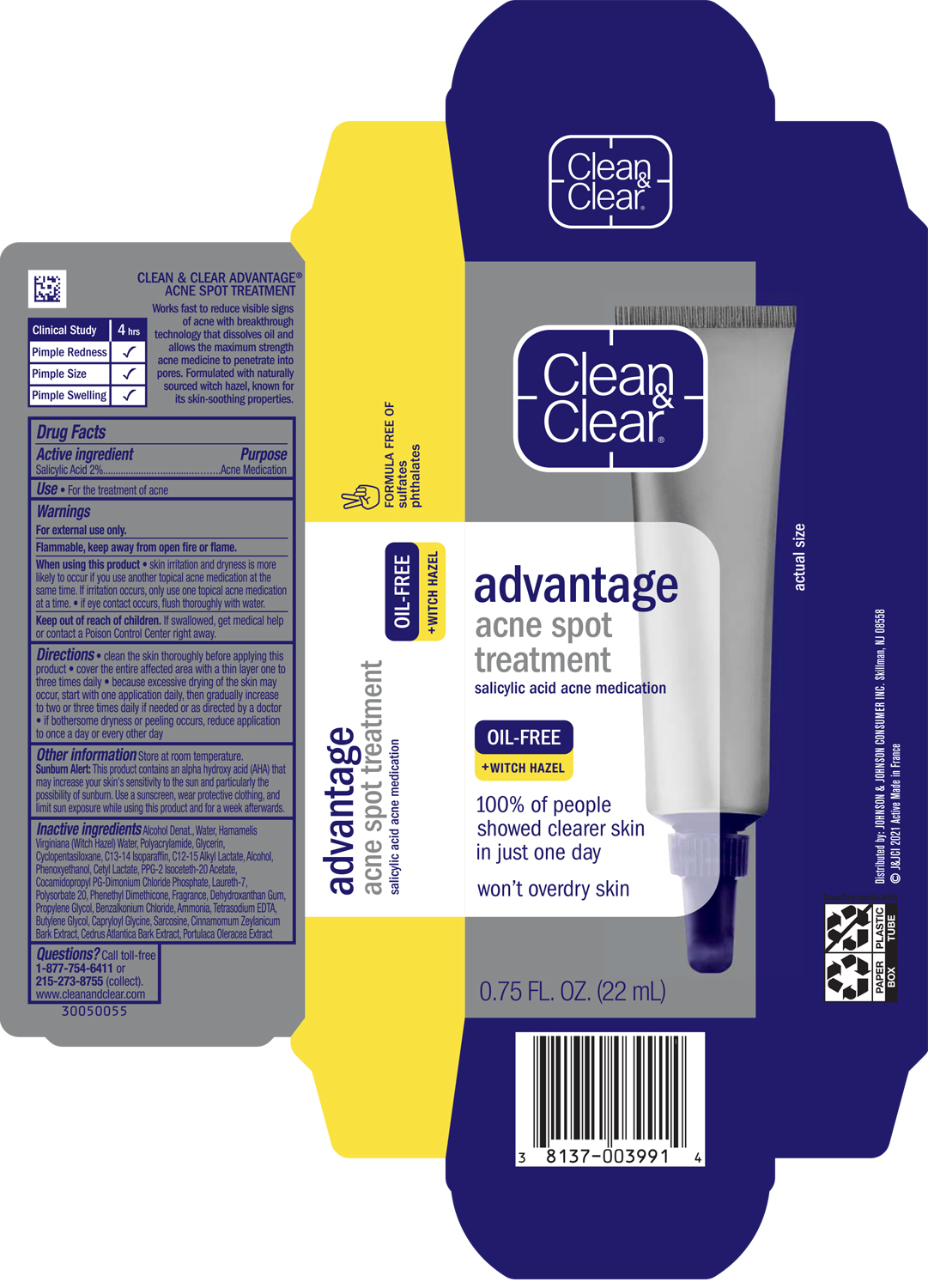 DRUG LABEL: Clean and Clear Advantage Acne Spot Treatment
NDC: 69968-0126 | Form: LOTION
Manufacturer: Kenvue Brands LLC
Category: otc | Type: HUMAN OTC DRUG LABEL
Date: 20241106

ACTIVE INGREDIENTS: SALICYLIC ACID 20 mg/1 mL
INACTIVE INGREDIENTS: WATER; WITCH HAZEL; GLYCERIN; CYCLOMETHICONE 5; C13-14 ISOPARAFFIN; C12-15 ALKYL LACTATE; ALCOHOL; PHENOXYETHANOL; CETYL LACTATE; PPG-2 ISOCETETH-20 ACETATE; COCAMIDOPROPYL PROPYLENE GLYCOL-DIMONIUM CHLORIDE PHOSPHATE; LAURETH-7; POLYSORBATE 20; DEHYDROXANTHAN GUM; PROPYLENE GLYCOL; BENZALKONIUM CHLORIDE; AMMONIA; EDETATE SODIUM; BUTYLENE GLYCOL; CAPRYLOYL GLYCINE; SARCOSINE; CINNAMON BARK OIL; CEDRUS ATLANTICA BARK; PURSLANE

Clean & Clear® advantage acne spot treatment

Drug Facts

Active Ingredient

Salicylic Acid (2%)

Purpose

Acne Medication

Use

- For the treatment of acne

Warnings

For external use only.

Flammable, keep away from open fire or flame.

When using this product

- skin irritation and dryness is more likely to occur if you use another topical acne medication at the same time. If irritation occurs, only use one topical acne medication at a time.
- If eye contact occurs, flush thoroughly with water.

Keep out of reach of children. If swallowed, get medical help or contact a Poison Control Center right away.

Directions

- clean the skin thoroughly before applying this product.
- cover the entire affected area with a thin layer one to three times daily
- because excessive drying of the skin may occur, start with one application daily, then gradually increase to two or three times daily if needed or as directed by a doctor
- if bothersome dryness or peeling occurs, reduce application to once a day or every other day

Other Information

Store at room temperature.

Sunburn Alert

This product contains an alpha hydroxy acid (AHA) that may increase your skin's sensitivity to the sun and particularly the possibility of sunburn. Use a sunscreen, wear protective clothing, and limit sun exposure while using this product and for a week afterwards.

Inactive Ingredients

Alcohol Denat., Water, Hamamelis Virginiana (Witch Hazel) Water, Polyacrylamide, Glycerin, Cyclopentasiloxane, C13-14 Isoparaffin, C12-15 Alkyl Lactate, Alcohol, Phenoxyethanol, Cetyl Lactate, PPG-2 Isoceteth-20 Acetate, Cocamidopropyl PG-Dimonium Chloride Phosphate, Laureth-7, Polysorbate 20, Phenethyl Dimethicone, Fragrance, Dehydroxanthan Gum, Propylene Glycol, Benzalkonium Chloride, Ammonia, Tetrasodium EDTA, Butylene Glycol, Capryloyl Glycine, Sarcosine, Cinnamomum, Zeylanicum Bark Extract, Cedrus Atlantica Bark Extract, Portulaca Oleracea Extract

Questions?

Call toll‐free 1-877-754-6411 or 215-273-8755 (collect).www.cleanandclear.com

Distributed by:
JOHNSON & JOHNSON CONSUMER INC.
Skillman, NJ 08558

PRINCIPAL DISPLAY PANEL - 22 mL Tube Carton

Clean
&
Clear®

advantage
acne spot
treatment
salicylic acid acne medication

OIL-FREE

+WITCH HAZEL

100% of people
showed clearer skin
in just one day

won't overdry skin

0.75 FL. OZ. (22mL)